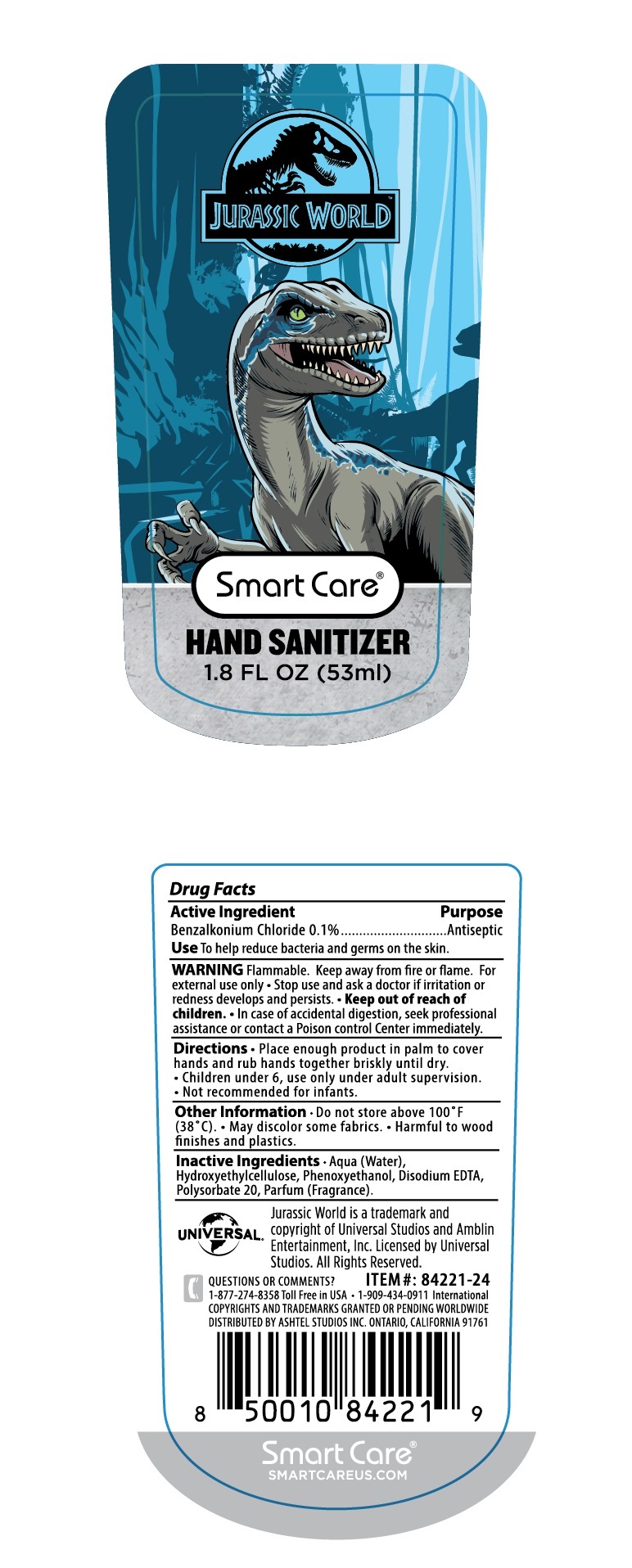 DRUG LABEL: JURASSIC WORLD HAND SANITIZER
NDC: 70108-026 | Form: LIQUID
Manufacturer: Ashtel Studios, Inc
Category: otc | Type: HUMAN OTC DRUG LABEL
Date: 20191105

ACTIVE INGREDIENTS: BENZALKONIUM CHLORIDE 0.1 g/100 mL
INACTIVE INGREDIENTS: WATER; HYDROXYETHYL CELLULOSE (4000 MPA.S AT 1%); PHENOXYETHANOL; EDETATE DISODIUM ANHYDROUS; POLYSORBATE 20

JURASSIC WORLD HAND SANITIZER

Active Ingredient

Benzalkonium Chloride 0.1%

Purpose

Antiseptic

INDICATIONS AND USAGE

Use To help reduce bacteria and germs on the skin.

WARNINGS

WARNING Flammable. Keep away from fire or flame. For external use only • Stop use and ask a doctor if irritation or redness develops and persists.

• Keep out of reach of children. •In case of accidental digestion, seek professional assistance or contact a Poison Control Center immediately.

DOSAGE AND ADMINISTRATION

Directions • Place enough product in palm to cover hands and rub hands together briskly until dry.

• Children under 6, use only under adult supervision.

• Not recommended for infants.

Other Information • Do not store above 100°F (38° C). • May discolor some fabrics. • Harmful to wood finishes and plastics.

INACTIVE INGREDIENT

Inactive Ingredients • Aqua (Water), Hydroxyethylcellulose, Phenoxyethanol, Disodium EDTA, Polysorbate 20, Parfum (Fragrance).

Jurassic World is a trademark and copyright of Universal Studios and Amblin Entertainment, Inc. Licensed by Universal Studios. All Rights Reserved.

QUESTIONS OR COMMENTS ?

1-877-274-8358 Toll Free in USA + 1-909-434-0911 International COPYRIGHTS AND TRADEMARKS GRANTED OR PENDING WORLDWIDE

DISTRIBUTED BY ASHTEL STUDIOS INC. ONTARIO, CALIFORNIA 91761

Smart Care®

SMARTCAREUS.COM